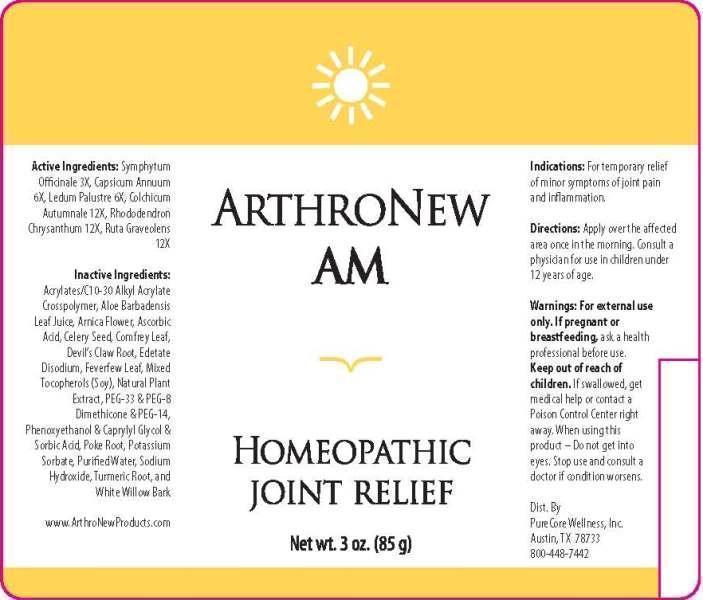 DRUG LABEL: ARTHRONEW
NDC: 61045-0001 | Form: GEL
Manufacturer: PureCore Wellness, Inc.
Category: homeopathic | Type: HUMAN OTC DRUG LABEL
Date: 20141106

ACTIVE INGREDIENTS: COMFREY ROOT 3 [hp_X]/1 g; CAPSICUM 6 [hp_X]/1 g; LEDUM PALUSTRE TWIG 6 [hp_X]/1 g; COLCHICUM AUTUMNALE BULB 12 [hp_X]/1 g; RHODODENDRON AUREUM LEAF 12 [hp_X]/1 g; RUTA GRAVEOLENS FLOWERING TOP 12 [hp_X]/1 g
INACTIVE INGREDIENTS: CARBOMER COPOLYMER TYPE A (ALLYL PENTAERYTHRITOL CROSSLINKED); ALOE VERA LEAF; ARNICA MONTANA FLOWER; ASCORBIC ACID; CELERY SEED; COMFREY LEAF; HARPAGOPHYTUM PROCUMBENS ROOT; EDETATE DISODIUM; FEVERFEW; .ALPHA.-TOCOPHEROL; OREGANO; POLYETHYLENE GLYCOL 1500; PEG-8 DIMETHICONE; POLYETHYLENE GLYCOL 700; PHENOXYETHANOL; CAPRYLYL GLYCOL; SORBIC ACID; PHYTOLACCA AMERICANA ROOT; POTASSIUM SORBATE; WATER; SODIUM HYDROXIDE; TURMERIC; SALIX ALBA BARK

DRUG FACTS:

ACTIVE INGREDIENTS:

SYMPHYTUM OFFICINALE 3X, CAPSICUM ANNUUM 6X, LEDUM PALUSTRE 6X, COLCHICUM AUTUMNALE 12X, RHODODENDRON CHRYSANTHUM 12X, RUTA GRAVEOLENS 12X

INDICATIONS:

For temporary relief of minor symptoms of joint pain and inflammation.

WARNINGS:

For external use only. If pregnant or breastfeeding, ask a health professional before use.

Keep out of reach of children. If swallowed, get medical help or contact a Poison Control Center right away.

When using this product - Do not get into eyes. Stop use and consult a doctor if condition worsens.

Keep out of reach of children. If swallowed, get medical help or contact a Poison Control Center right away.

DIRECTIONS:

Apply over the affected area once in the morning. Consult a physician for use in children under 12 years of age.

INDICATIONS:

For temporary relief of minor symptoms of joint pain and inflammation.

INACTIVE INGREDIENTS:

ACRYLATES/C10-30 ALKYL ACRYLATE CROSSPOLYMER, ALOE BARBADENSIS LEAF JUICE, ARNICA (FLOWER), ASCORBIC ACID, CELERY (SEED), COMFREY (LEAF), DEVIL'S CLAW (ROOT), EDETATE DISODIUM (EDTA), FEVERFEW (LEAF), MIXED TOCOPHEROLS [VITAMIN E] (DERIVED FROM SOY BEAN), NATURAL PLANT EXTRACT, PEG-33, PEG-8 DIMETHICONE, PEG-14, PHENOXYETHANOL, CAPRYLYL GLYCOL, SORBIC ACID, POKE (ROOT), POTASSIUM SORBATE, PURIFIED WATER, SODIUM HYDROXIDE, TURMERIC (ROOT), WHITE WILLOW (BARK)

QUESTIONS:

Dist. By

PureCore Wellness, Inc.

Austin, TX 78733

800-448-7442

www.ArthroNewProducts.com

PACKAGE LABEL DISPLAY:

ARTHRONEW

AM

HOMEOPATHIC

JOINT RELIEF

Net wt. 3 oz. (85 g)